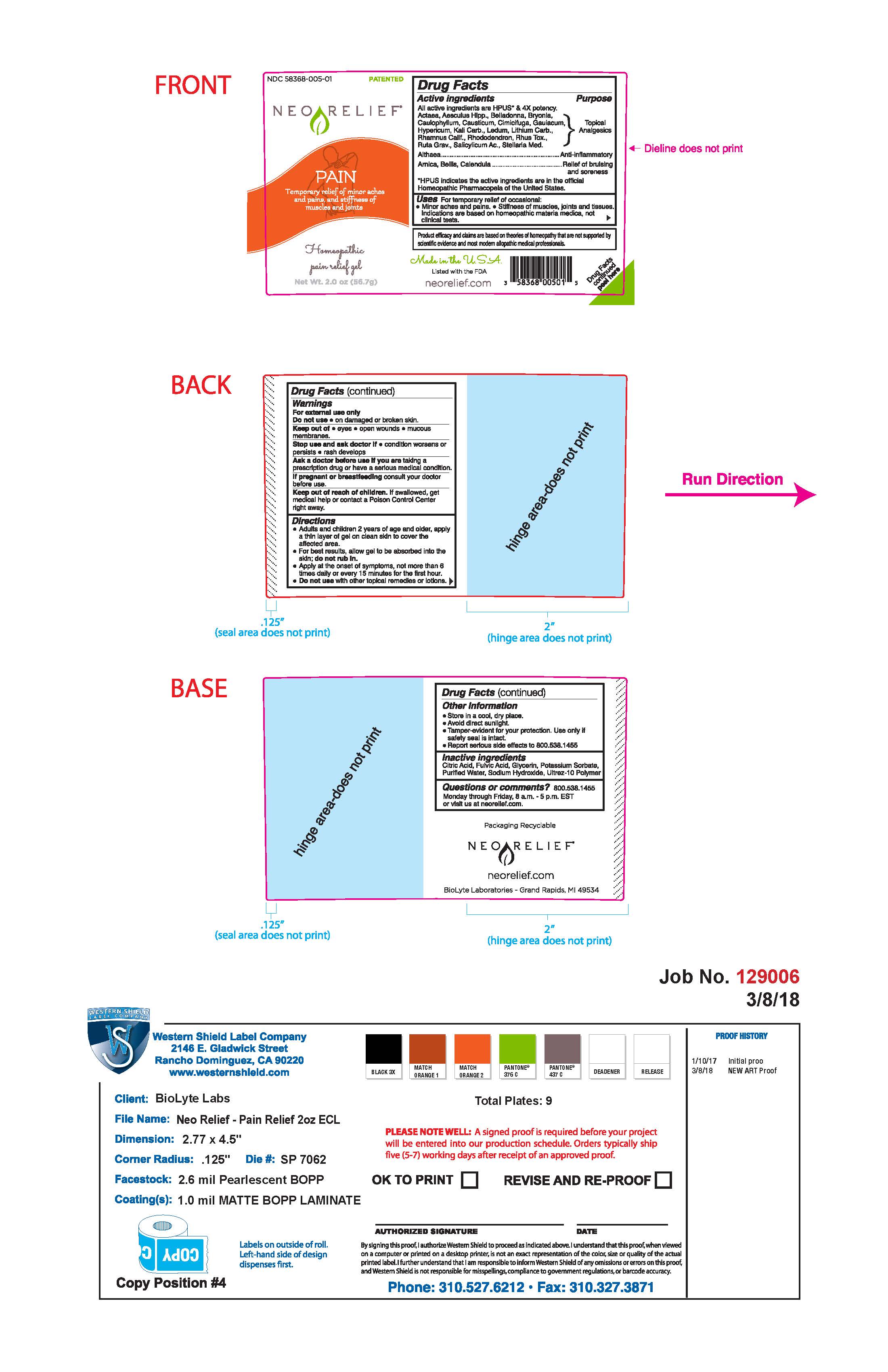 DRUG LABEL: NEORELIEF FOR PAIN
NDC: 58368-005 | Form: GEL
Manufacturer: BioLyte Laboratories, LLC
Category: homeopathic | Type: HUMAN OTC DRUG LABEL
Date: 20260127

ACTIVE INGREDIENTS: BELLIS PERENNIS 4 [hp_X]/1 g; BRYONIA ALBA ROOT 4 [hp_X]/1 g; CALENDULA OFFICINALIS FLOWERING TOP 4 [hp_X]/1 g; CAULOPHYLLUM THALICTROIDES ROOT 4 [hp_X]/1 g; CAUSTICUM 4 [hp_X]/1 g; GUAIACUM OFFICINALE RESIN 4 [hp_X]/1 g; HYPERICUM PERFORATUM 4 [hp_X]/1 g; LITHIUM CARBONATE 4 [hp_X]/1 g; FRANGULA CALIFORNICA BARK 4 [hp_X]/1 g; RHODODENDRON AUREUM LEAF 4 [hp_X]/1 g; TOXICODENDRON PUBESCENS LEAF 4 [hp_X]/1 g; RUTA GRAVEOLENS FLOWERING TOP 4 [hp_X]/1 g; HORSE CHESTNUT 4 [hp_X]/1 g; SALICYLIC ACID 4 [hp_X]/1 g; BLACK COHOSH 4 [hp_X]/1 g; STELLARIA MEDIA 4 [hp_X]/1 g; ACTAEA SPICATA ROOT 4 [hp_X]/1 g; ALTHAEA OFFICINALIS ROOT 4 [hp_X]/1 g; ARNICA MONTANA 4 [hp_X]/1 g; ATROPA BELLADONNA ROOT 4 [hp_X]/1 g; POTASSIUM CARBONATE 4 [hp_X]/1 g; LEDUM PALUSTRE TWIG 4 [hp_X]/1 g
INACTIVE INGREDIENTS: CARBOMER HOMOPOLYMER TYPE C (ALLYL PENTAERYTHRITOL CROSSLINKED); CITRIC ACID MONOHYDRATE; FULVIC ACID; POTASSIUM SORBATE; SODIUM HYDROXIDE; WATER; GLYCERIN

Drug Facts Active Ingredients

All active ingredients are HPUS* and 4X potency

Actaea, Aesculus Hipp., Belladonna, Bryonia., Caulophyllum, Causticum, Cimicifuga, Gauiacum, Hypericum, Kali Carb., Ledum, Lithium Carb., Rhamnus Calif., Rhododendron, Rhus. Tox., Ruta Grav., Salicylicum Ac., Setllaria Med.

Althaea

Arnica, Bellis, Calendula

Purpose

Topical Analgesics

Anti-inflammatory

Relief of bruising and soreness

Uses

For temporary relief of occasional:

Minor aches and pains

Stiffness of muscles, joints, and tissues

Indications are based on homeopathic materia medica, not clinical tests.

Warnings

For external use only

Do not use on damaged or broken skin.

Keep out of eyes, open wounds, mucous membranes.

Warnings

Stop use and ask doctor if condition worsens or persists, rash develeops

Warnings

Ask a doctor before use if you are taking a prescription drug or have a serious medical condition.

Warnings

If pregnant or breatfeeding consult your doctor before use.

Warnings

Keep out of reach of children. If swallowed, get medical help or contact a Poison Control Center right away.

Directions

- Adults and children 2 years of age and older, apply a thin layer of gel on clean skin to cover the affected area.
- For best results, allow gel to be absorbed into the skin; do not rub in.
- Apply at the onset of symptoms, not more than 6 times daily or every 15 minutes for the first hour.
- Do not use with other topical remedies or lotions.

Other Information

- Store in a cool, dry place.
- Avoid direct sunlight.
- Tamper-evident for your protection. Use only if safety seal is intact.
- Report all serious side effects to 800.538.1455

Inactive Ingredients

Citric Acid, Fulvic Acid, Glycerin, Potassium Sorbate, Purified Water, Sodium Hydroxide, Ultrez-10 Polymer

Questions or comments?

800.538.1455

Monday through Friday 8 a.m. - 5 p.m. EST or visit us at neorelief.com

Additional Label Content

Required FTC Disclosure: Product efficacy and claims are based on theories of homeopathy that are not supported by scientific evidence and most modern allopathic medical professionals.

Made in the USA

Listed with the FDA

(UPC code: 3 58368 00501 5)

Drug Facts continued Peel Here

Packaging Recyclable

neorelief.com

BioLyte laboratories- Grand Rapids, MI 49534

NEORELIEF for PAIN 56.7g Bottle

NDC 58368-005-01 Patented

NeoRelief

Pain

Temporary relief of minor aches and pains, and stiffness of muscles and joints

Homeopathic

pain relief gel

Net Wt. 2.0 oz (56.7g)